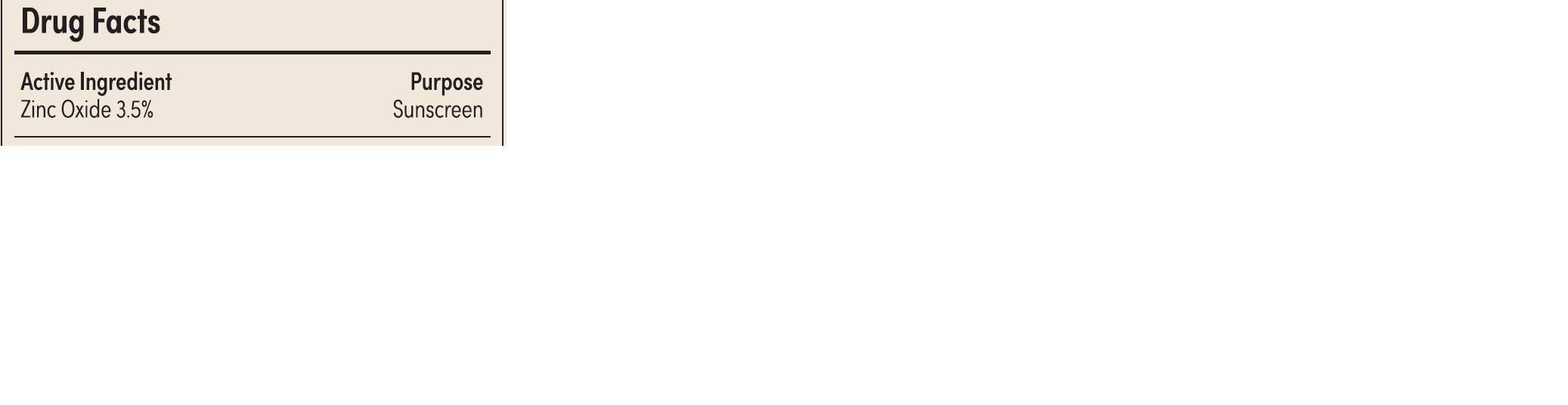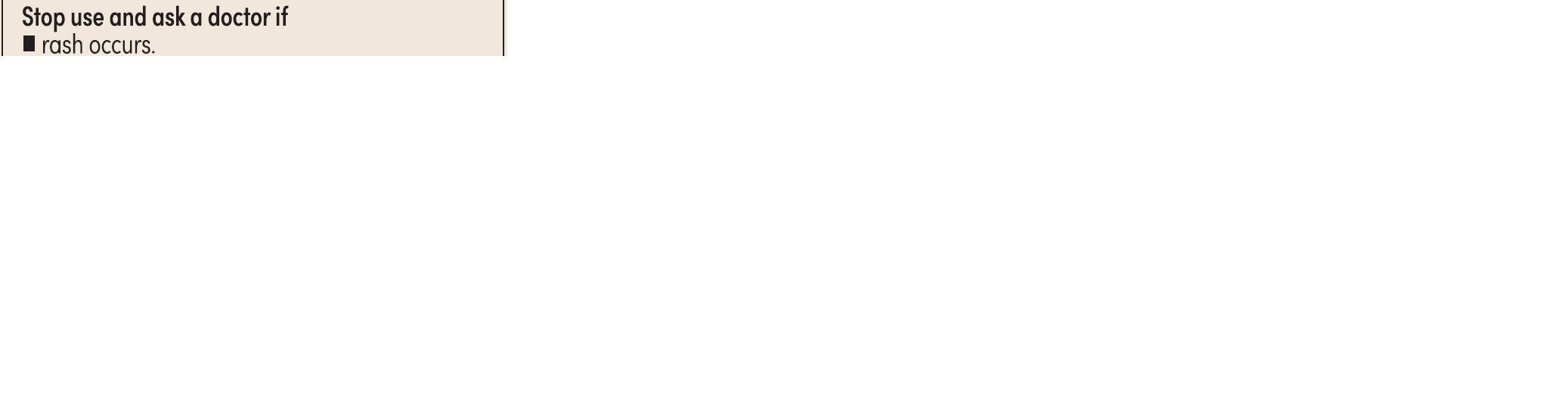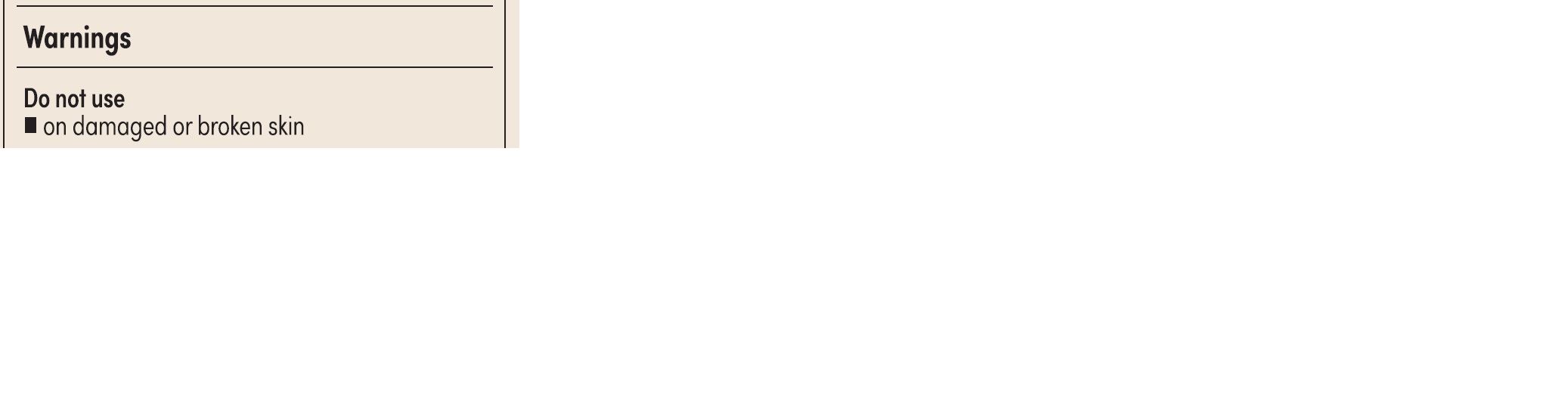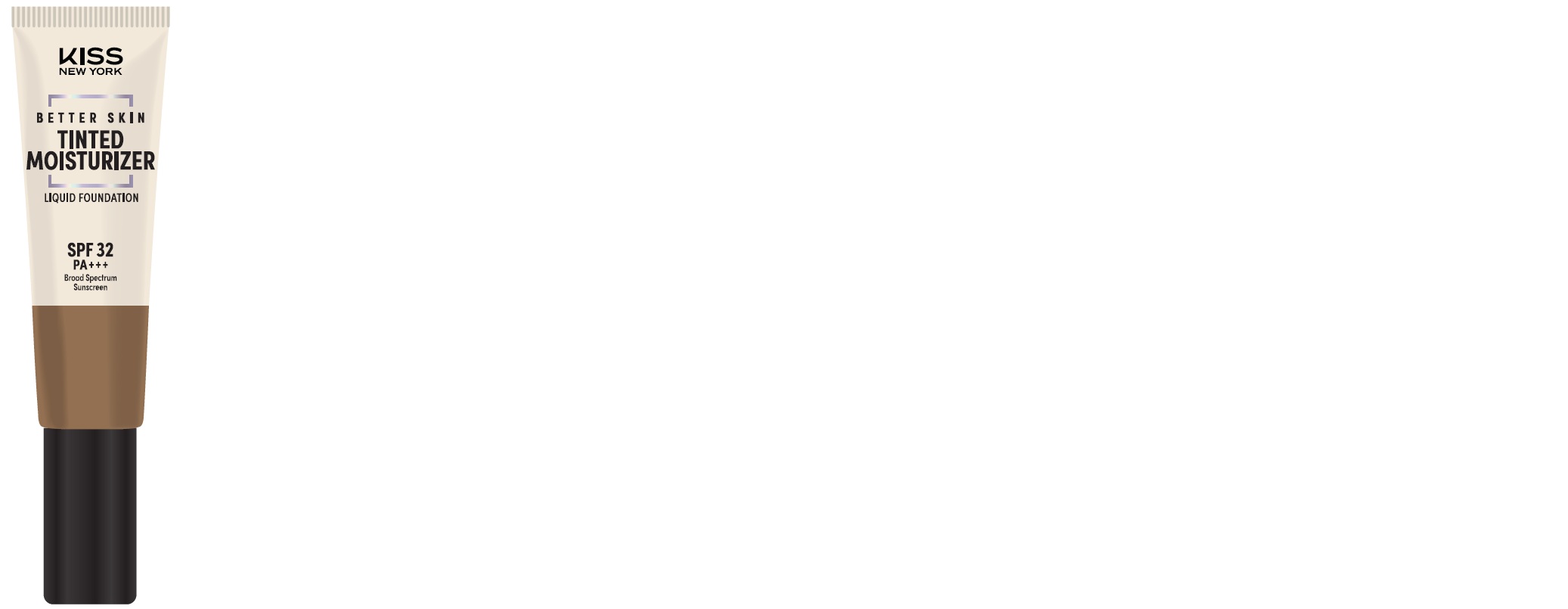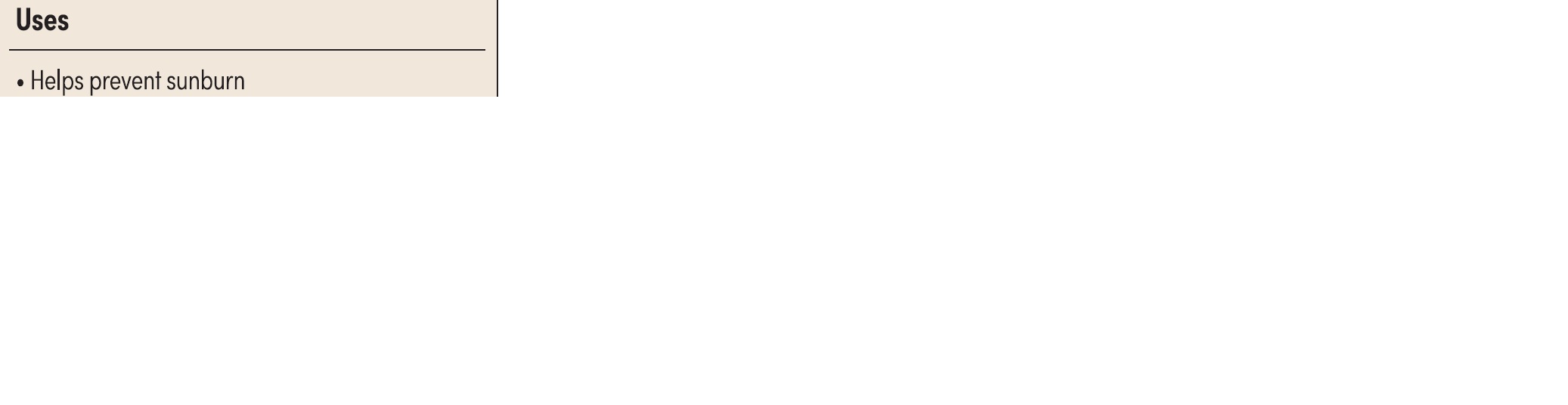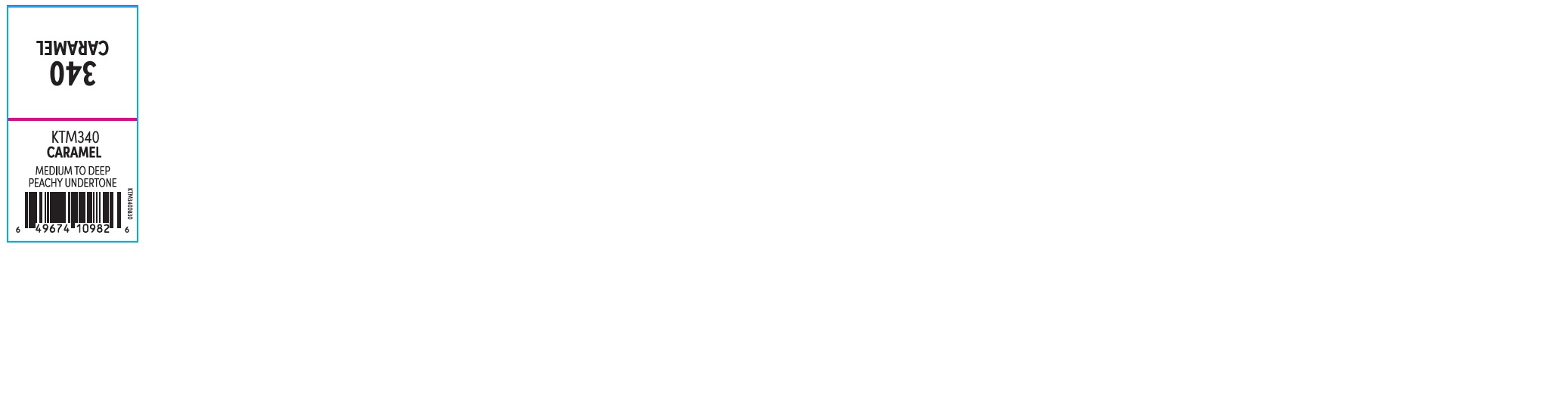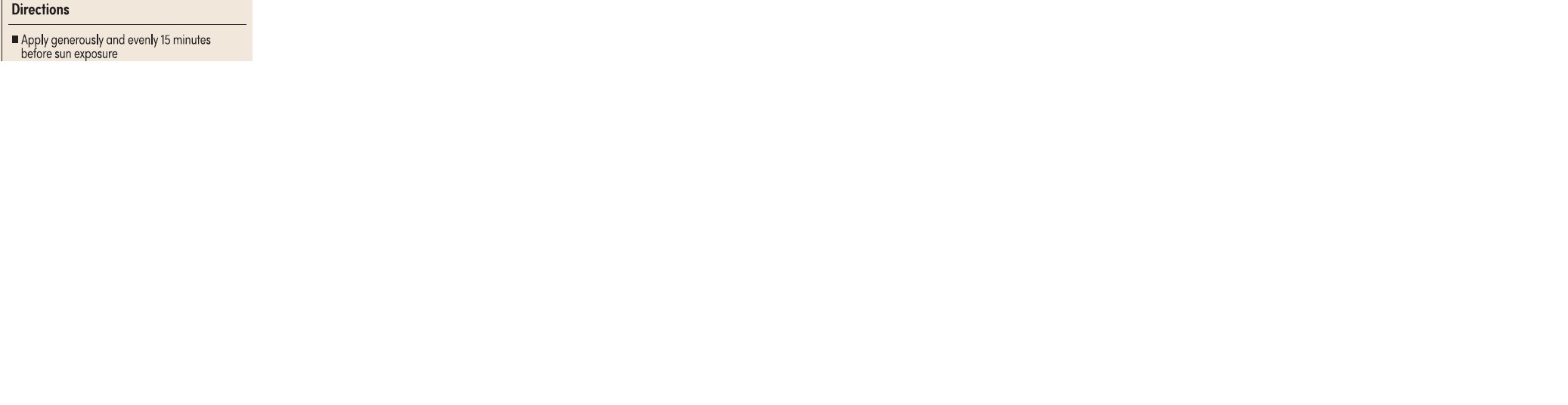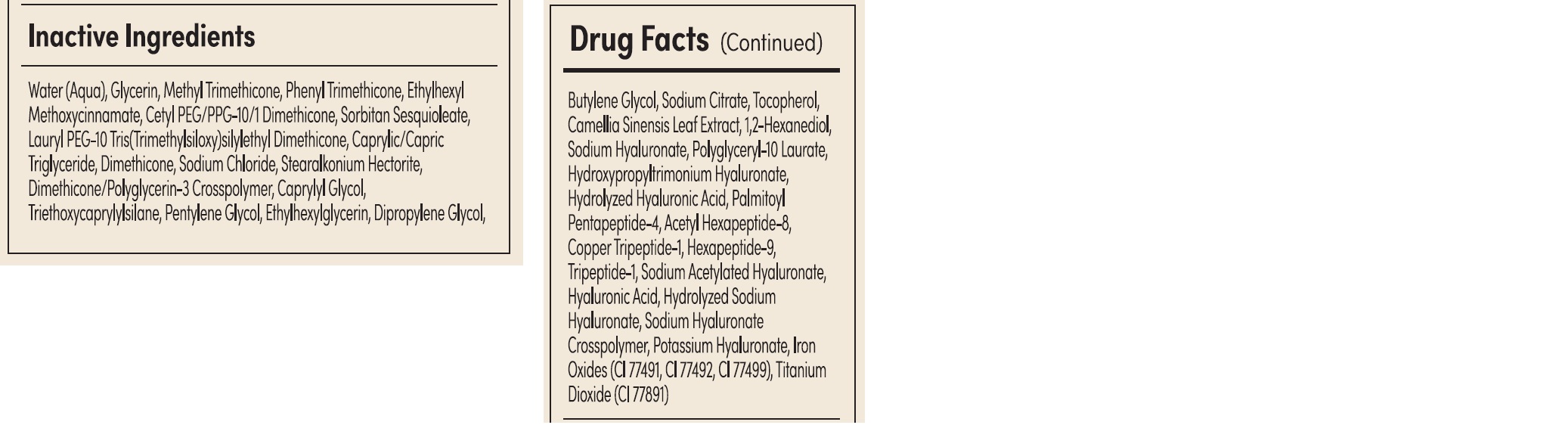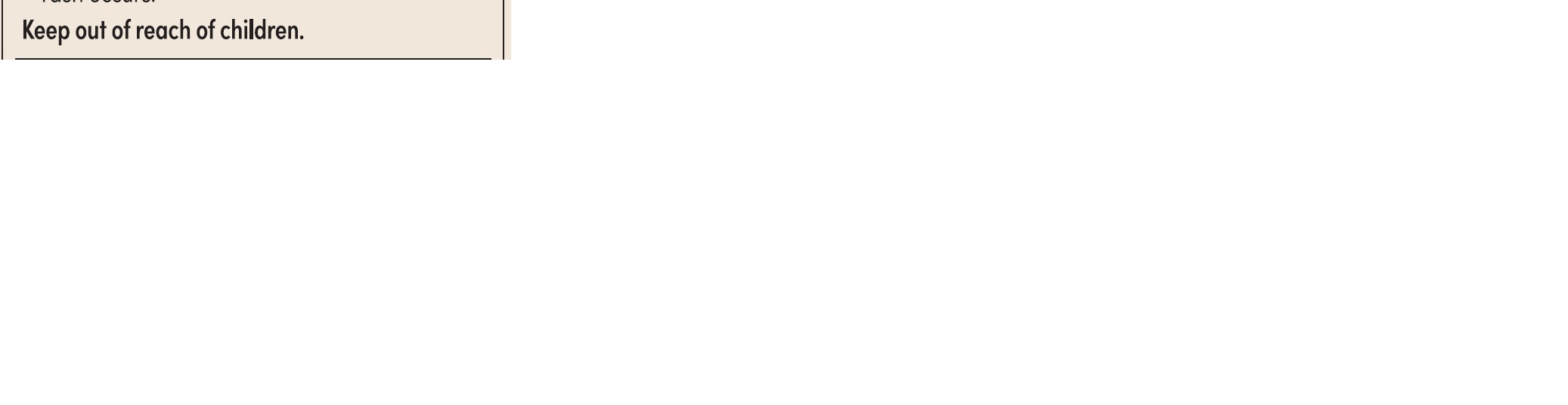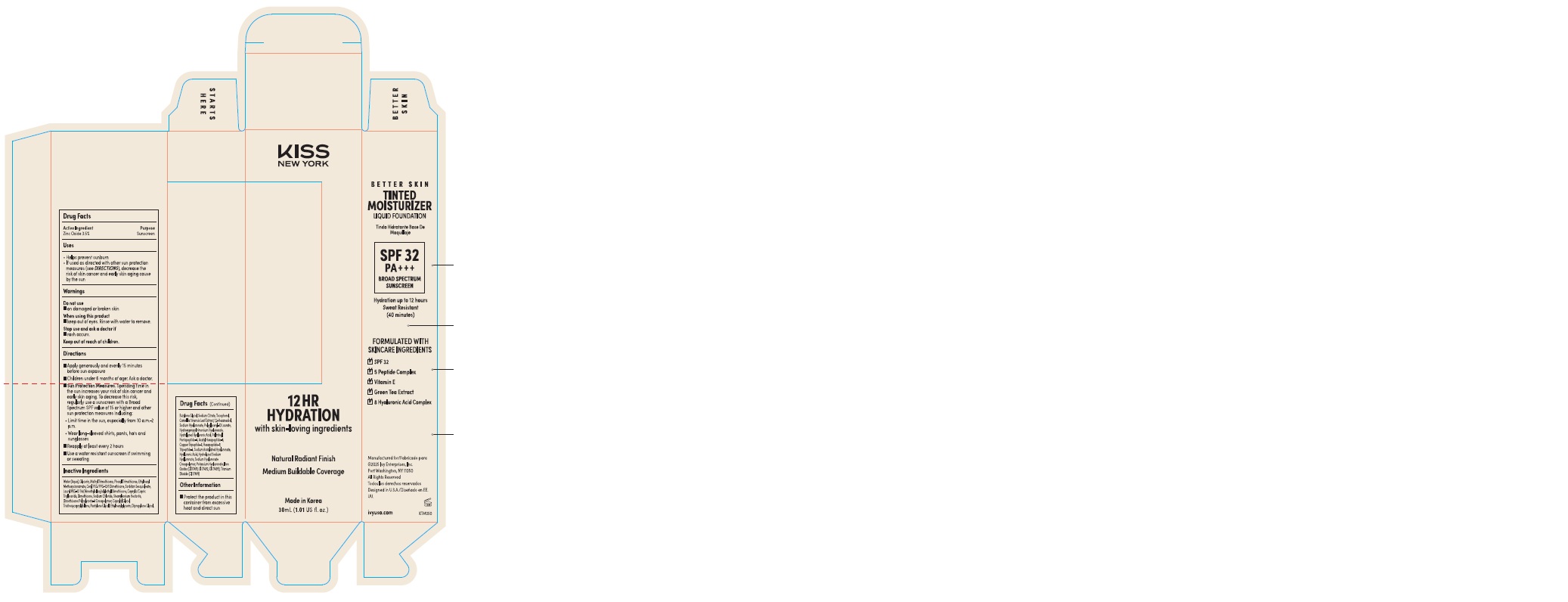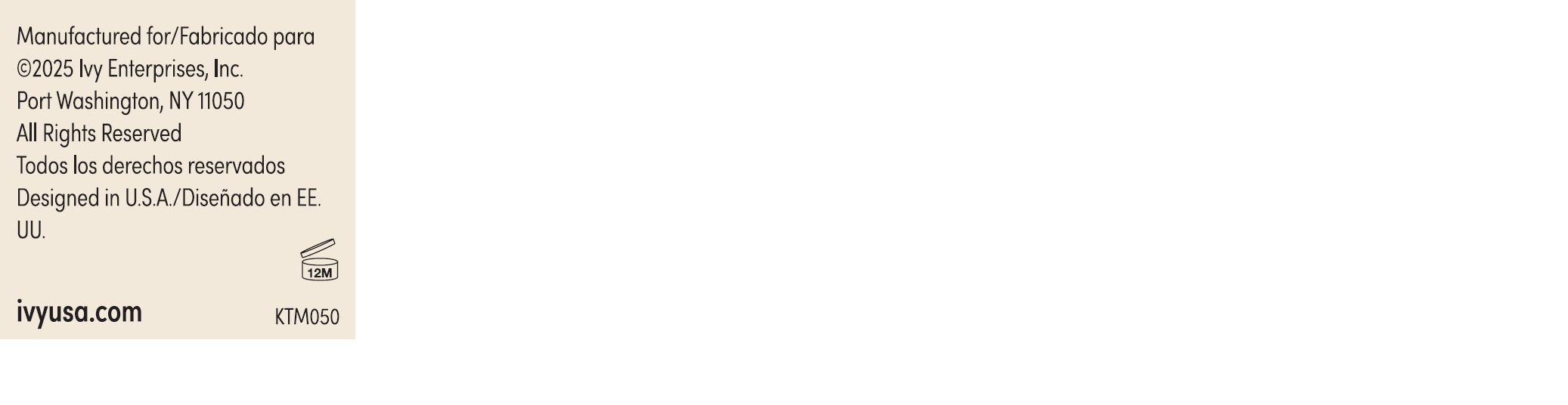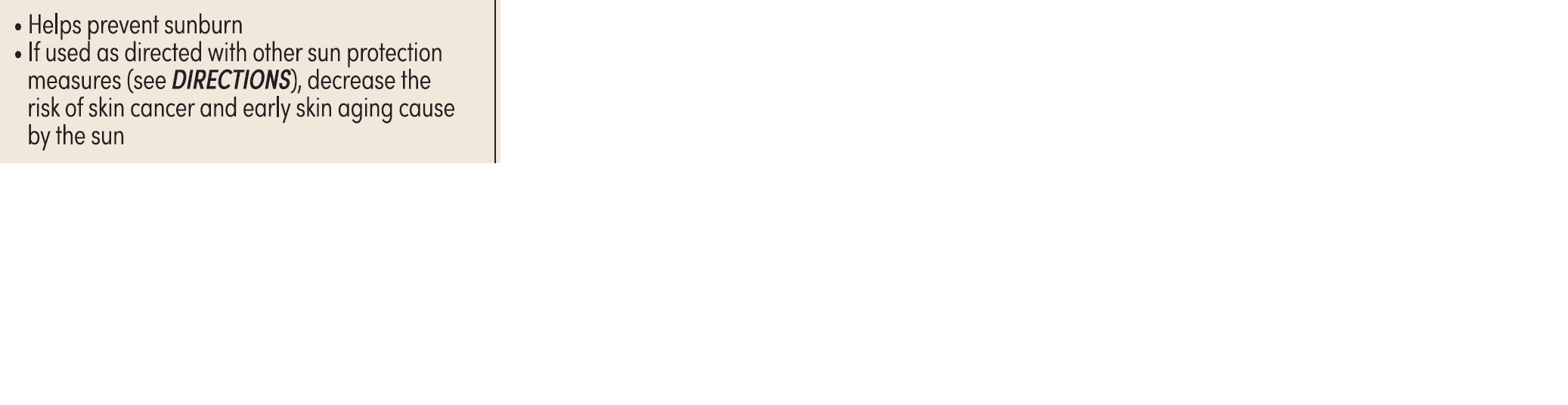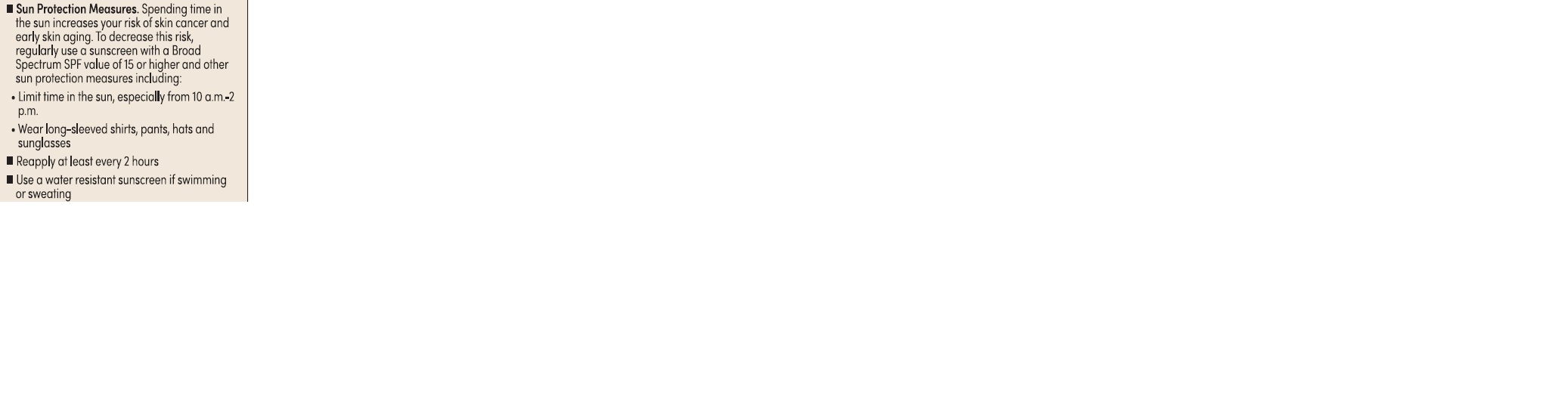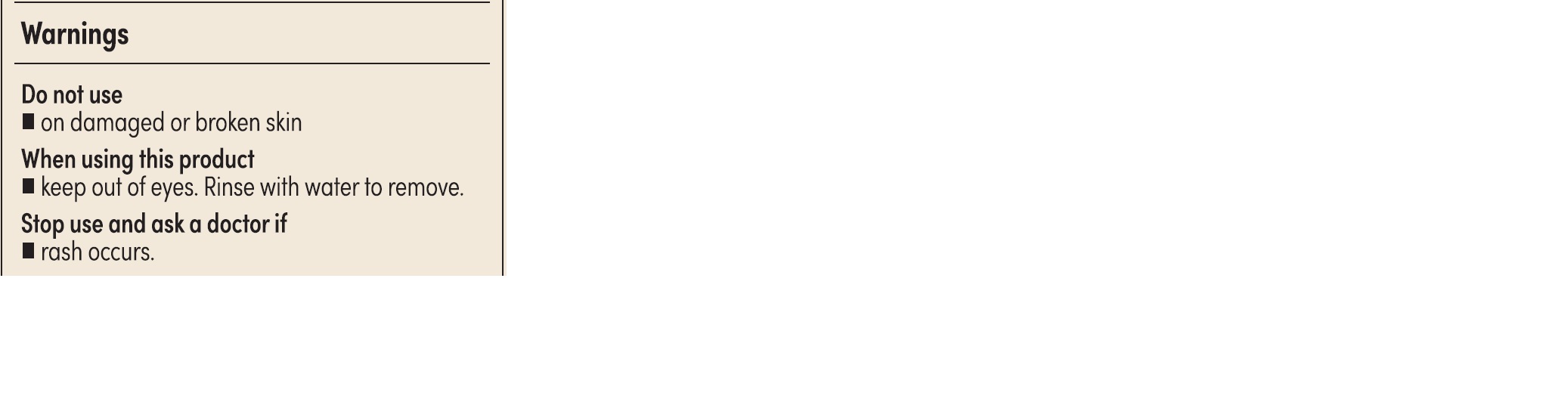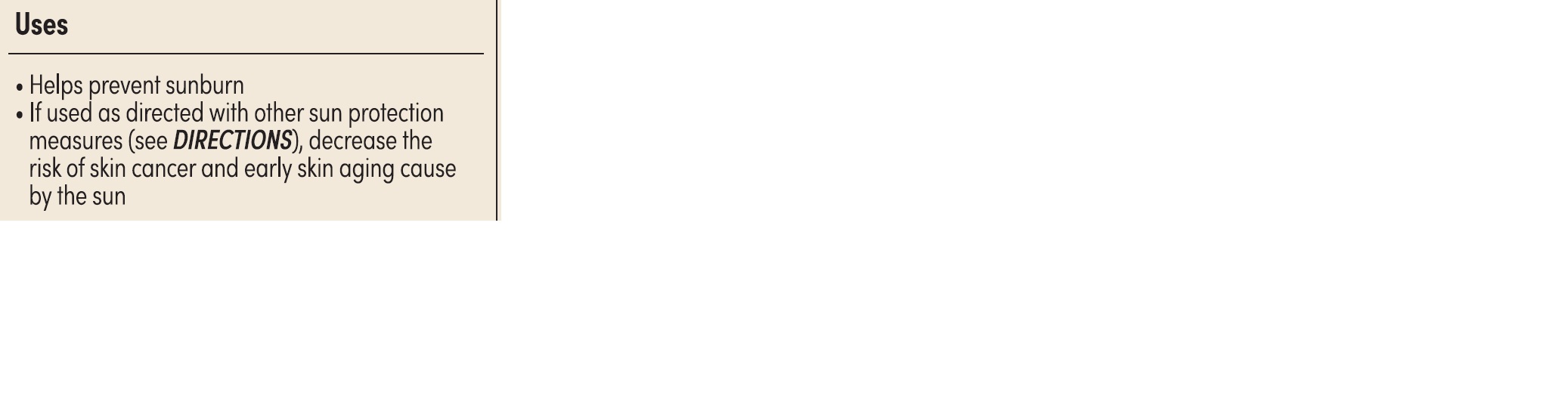 DRUG LABEL: KISS New York Tinted Moisturizer
NDC: 79906-340 | Form: CREAM
Manufacturer: IVY ENTERPRISES, INC.
Category: otc | Type: HUMAN OTC DRUG LABEL
Date: 20250324

ACTIVE INGREDIENTS: ZINC OXIDE 3.5 g/100 g
INACTIVE INGREDIENTS: DIMETHYLSILANOL HYALURONATE; TITANIUM DIOXIDE; METHYL TRIMETHICONE; ACETYL HEXAPEPTIDE-8; DIMETHICONE; PHENYL TRIMETHICONE; PENTYLENE GLYCOL; 1,2-HEXANEDIOL; PALMITOYL PENTAPEPTIDE-4; TRIPEPTIDE-1; TOCOPHEROL; ETHYLHEXYL METHOXYCINNAMATE; STEARALKONIUM HECTORITE; SODIUM CITRATE; SODIUM HYALURONATE; BUTYLENE GLYCOL; CETYL PEG/PPG-10/1 DIMETHICONE (HLB 2); CAPRYLIC/CAPRIC TRIGLYCERIDE; CI 77492; CI 77491; POLYGLYCERYL-10 LAURATE; CAMELLIA SINENSIS LEAF; CI 77499; WATER; DIMETHICONE/POLYGLYCERIN-3 CROSSPOLYMER; DIPROPYLENE GLYCOL; TRIETHOXYCAPRYLYLSILANE; COPPER TRIPEPTIDE-1; GLYCERIN; PEG-10 DIMETHICONE (600 CST); SODIUM CHLORIDE; ETHYLHEXYLGLYCERIN; HYALURONIC ACID; HEXAPEPTIDE-9; SODIUM ACETYLATED HYALURONATE; PEG-9 DIGLYCIDYL ETHER/SODIUM HYALURONATE CROSSPOLYMER; SORBITAN SESQUIOLEATE; CAPRYLYL GLYCOL

Kiss New York Tinted Moisturizer KTM340 CARAMEL